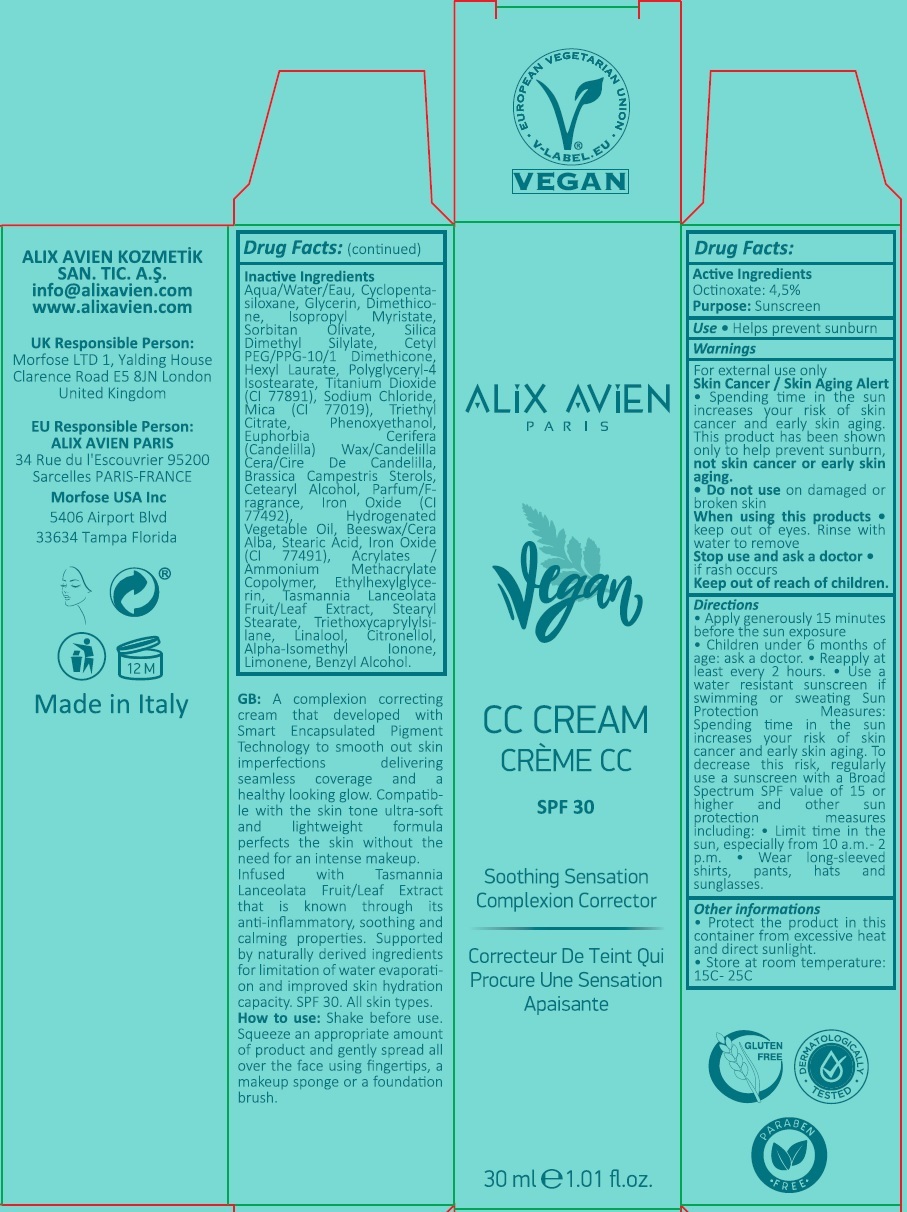 DRUG LABEL: Alix Avien
NDC: 82668-100 | Form: CREAM
Manufacturer: ALIX AVIEN KOZMETIK SANAYI TICARET ANONIM SIRKETI
Category: otc | Type: HUMAN OTC DRUG LABEL
Date: 20220407

ACTIVE INGREDIENTS: OCTINOXATE 45 mg/1 mL
INACTIVE INGREDIENTS: WATER; CYCLOMETHICONE 5; GLYCERIN; DIMETHICONE; ISOPROPYL MYRISTATE; SORBITAN OLIVATE; SILICA DIMETHYL SILYLATE; CETYL PEG/PPG-10/1 DIMETHICONE (HLB 2); HEXYL LAURATE; POLYGLYCERYL-4 ISOSTEARATE; TITANIUM DIOXIDE; SODIUM CHLORIDE; MICA; TRIETHYL CITRATE; PHENOXYETHANOL; CANDELILLA WAX; RAPESEED STEROL; CETOSTEARYL ALCOHOL; FERRIC OXIDE YELLOW; HYDROGENATED PALM OIL; YELLOW WAX; STEARIC ACID; FERRIC OXIDE RED; 2-(TRIMETHYLAMMONIO)ETHYL METHACRYLATE CHLORIDE; ETHYLHEXYLGLYCERIN; TASMANNIA LANCEOLATA FRUIT; TASMANNIA LANCEOLATA LEAF; STEARYL STEARATE; TRIETHOXYCAPRYLYLSILANE; LINALOOL, (+/-)-; .BETA.-CITRONELLOL, (R)-; ISOMETHYL-.ALPHA.-IONONE; LIMONENE, (+)-; BENZYL ALCOHOL

ALIX AVIEN Vegan CC CREAM SPF 30

Active Ingredients

Octinoxate: 4.5%

Purpose:

Sunscreen

Use

• Helps prevent sunburn

Warnings

For external use only

Skin Cancer / Skin Aging Alert • Spending time in the sun increases your risk of skin cancer and early skin aging. This product has been shown only to help prevent sunburn, not skin cancer or early skin aging.

• Do not use on damaged or broken skin

When using this products • keep out of eyes. Rinse with water to remove.

Stop use and ask a doctor • if rash occurs

Keep out of reach of children.

Directions

• Apply generously 15 minutes before the sun exposure
• Children under 6 months of age: ask a doctor. • Reapply at least every 2 hours. • Use a water resistant sunscreen if swimming or sweating Sun Protection Measures: Spending time in the sun increases your risk of skin cancer and early skin aging. To decrease this risk, regularly use a sunscreen with a Broad Spectrum SPF value of 15 or higher ad other sun protection measures including: • Limit time in the sun, especially from 10 a.m.- 2 p.m. • Wear long-sleeved shirts, pants, hats and sunglasses.

Other information

• Protect the product in this container from excessive heat and direct sunlight.
• Store at room temperature: 15C - 25C

Inactive Ingredients

Aqua/Water/Eau, Cyclopentasiloxane, Glycerin, Dimethicone, Isopropyl Myristate, Sorbitan Olivate, Silica Dimethyl Silylate, Cetyl PEG/PPG-10/1 Dimethicone, Hexyl Laurate, Polyglyceryl-4 Isostearate, Titanium Dioxide(CI 77891), Sodium Chloride, Mica (CI 77019), Triethyl Citrate, Phenoxyethanol, Euphorbia Cerifera (Candelilla) Wax/Candelilla Cera/Cire De Candelilla, Brassica Campestris Sterols, Cetearyl Alcohol, Parfum/Fragrance, Iron Oxide (CI 77492), Hydrogenated Vegetable Oil, Beeswax/Cera Alba, Stearic Acid, Iron Oxide (CI 77491), Acrylates / Ammonium Methacrylate Copolymer, Ethylhexylglycerin, Tasmannia Lanceolata Fruit/Leaf Extract, Stearyl Stearate, Triethoxycaprylylsilane, Linalool, Citronellol, Alpha-Isomethyl Ionone, Limonene, Benzyl Alcohol.

SPF 30

Soothing Sensation
Complexion Corrector

GB: A complexion correcting cream that developed with Smart Encapsulated Pigment Technology to smooth out skin imperfections delivering seamless coverage and a healthy looking glow. Compatible with the skin tone ultra-soft and lightweight formula perfects the skin without the need for an intense makeup. Infused with Tasmannia Lanceolata Fruit/Leaf Extract that is known through its anti-inflammatory, soothing and calming properties. Supported by naturally derived ingredients for limitation of water evaporation and improved skin hydration capacity SPF 30. All skin types.

How to use: Shake before use. Squeeze an appropriate amount of product and gently spread all over the face using fingertips, a makeup sponge or a foundation brush.

EUROPEAN VEGETARIAN UNION • V-LABEL.EU •

GLUTEN FREE

DERMATOLOGICALLY TESTED

PARABEN FREE

ALIX AVIEN KOZMETIK SAN. TIC. A.S.
info@alixavien.com
www.alixavien.com

UK Responsible Person:
Morfose LTD 1, Yalding House
Clarence Road E5 8JN London
United Kingdom

EU Responsible Person:
ALIX AVIEN PARIS
34 Rue du l'Escouvrier 95200
Sarcelles PARIS-FRANCE

Morfose USA Inc
5406 Airport Blvd
33634 Tampa Florida

Made in Italy